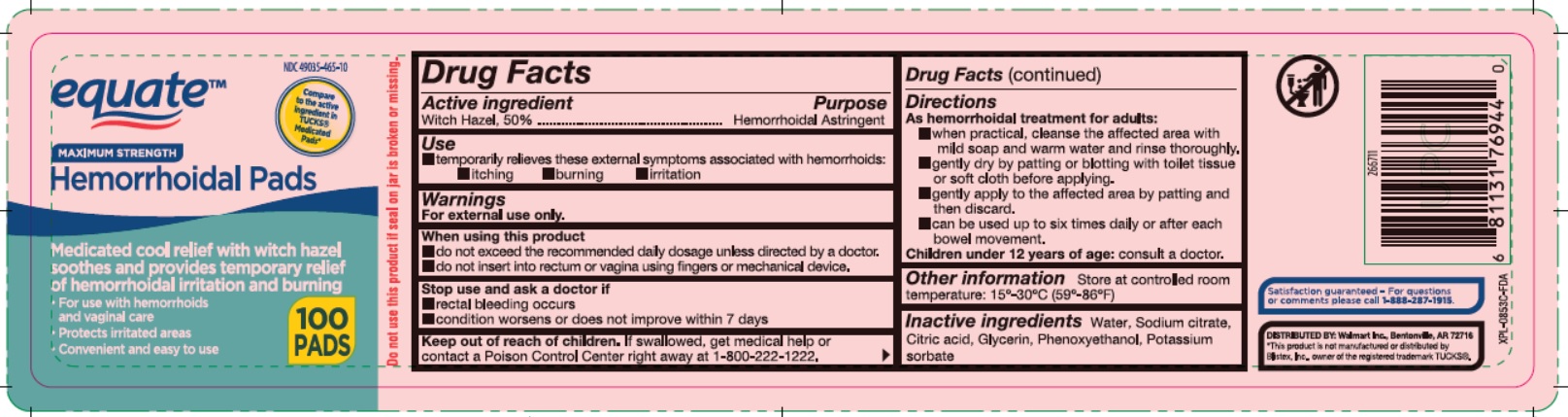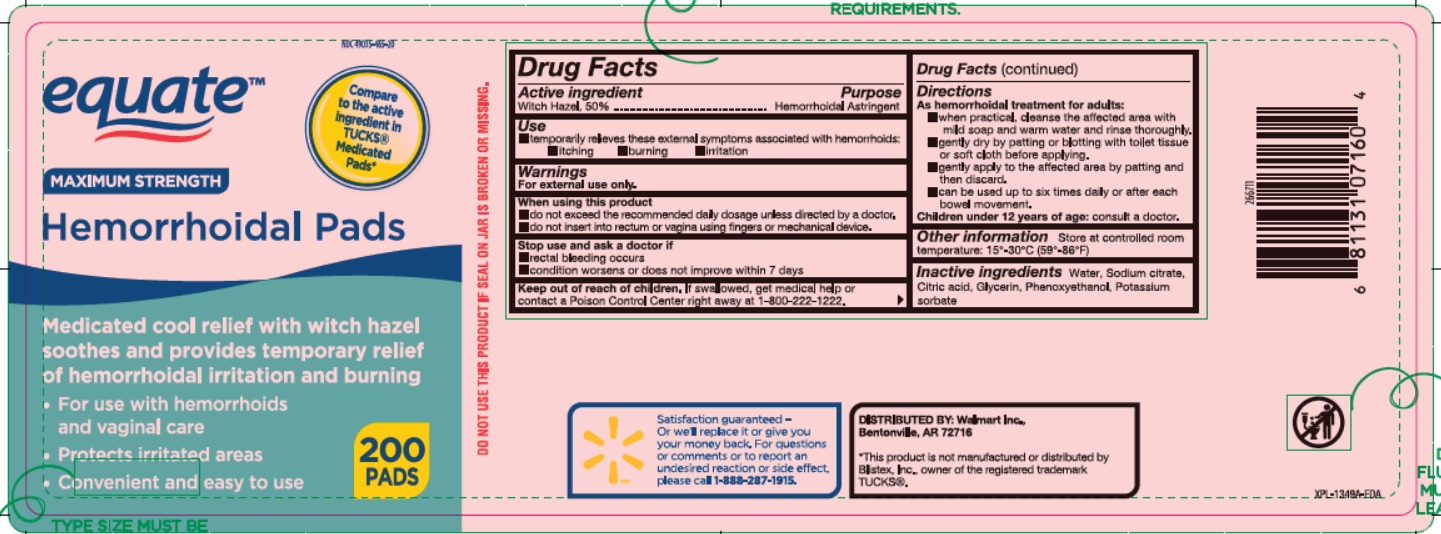 DRUG LABEL: Maximum Strength Hemorrhoidal Pads
NDC: 49035-465 | Form: CLOTH
Manufacturer: Walmart, Inc.
Category: otc | Type: HUMAN OTC DRUG LABEL
Date: 20250714

ACTIVE INGREDIENTS: WITCH HAZEL 500 mg/1 1
INACTIVE INGREDIENTS: WATER; SODIUM CITRATE; CITRIC ACID MONOHYDRATE; GLYCERIN; PHENOXYETHANOL; POTASSIUM SORBATE

Drug Facts

Active ingredient

Witch hazel 50%

Purpose

Hemorrhoidal Astringent

Uses

temporarily relieves these external symptoms associated with hemorrhoids:

- itching
- burning
- irritation

Warnings

For external use only.

When using this product

- do not exceed the recommended daily dosage unless directed by a doctor
- do not insert into rectum or vagina using fingers or any mechanical device.

Stop use and ask a doctor if

- rectal bleeding occurs
- condition worsens or does not improve within 7 days

Keep out of reach of children.

If swallowed, get medical help or contact Poison Control Center right away. (1-800-222-1222).

Directions

As hemorrhoidal treatment for adults:

- when practial cleanse the affected area with mild soap and warm water, and rinse thoroughly
- gently dry by patting or blotting with toilet tissue or soft cloth before applying.
- gently apply to the affected area by patting and then discard
- can be used up to six times daily or after each bowel movement

children under 12 years of age:consult a doctor

Other information

- store at controlled room temperature 15^0- 30oC (59^0- 86oF)

Inactive ingredients

Water, Sodium Citrate, Citric Acid, Glycerin, Phenoxyethanol, Potassium Sorbate.

Questions or Comments?

Satisfaction Guaranteed - Or we'll replace it Or give you your money back. For questions or comment or to report an undesired reaction or side effect please call 1-888-287-1915

Principal Display Panel

NDC 49035-465-10

equateTM

Maximum Strength Hemorrhoidal Pads

Compare to the active ingredient in TUCKS®Medicated Pads*

Medicated cool relief with witch hazel soothes and provides temporary relief of hemorrhoidal irritation and burning

- For use with hemorrhoids and vaginal care
- Protects irritated areas
- Convenient and easy to use

100 PADS

NDC 49035-465-20

equateTM

Maximum Strength Hemorrhoidal Pads

Compare to the active ingredient in TUCKS® Medicated Pads*

Medicated cool relief with witch hazel soothes and provides temporary relief of hemorrhoidal irritation and burning

- For use with hemorrhoids and vaginal care
- Protects irritated areas
- Convenient and easy to use

200 PADS